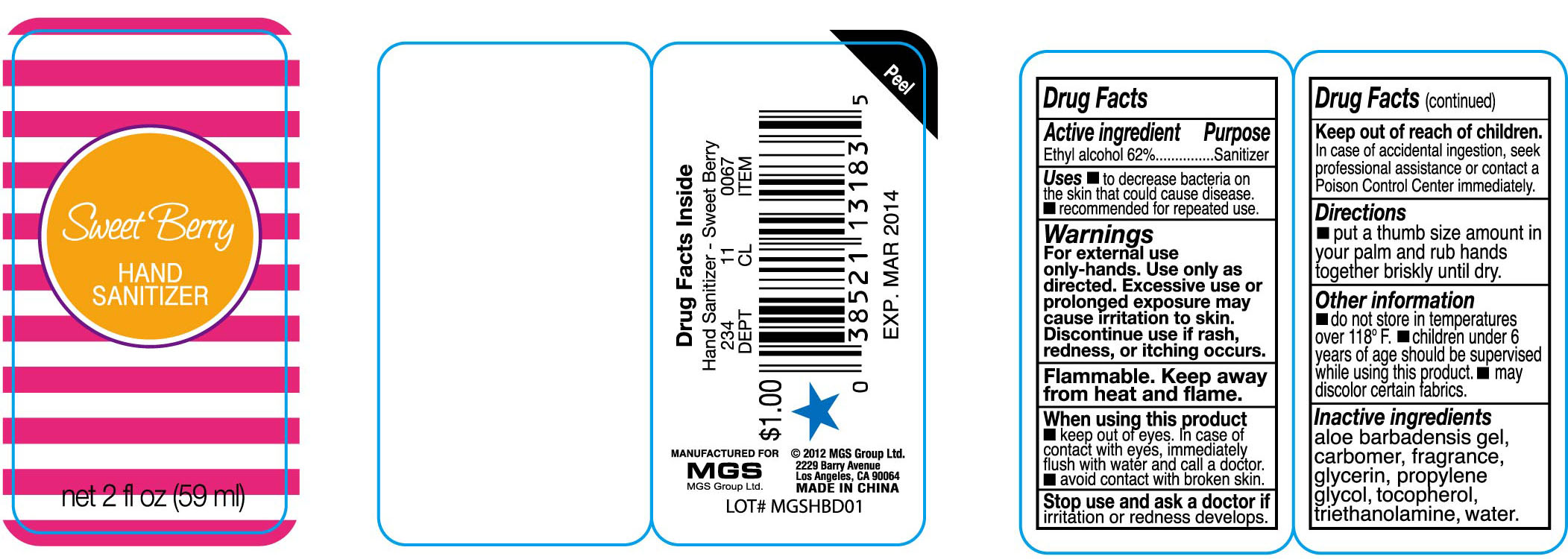 DRUG LABEL: Sweet Berry Hand Sanitizer
NDC: 51263-3183 | Form: GEL
Manufacturer: MGS Group Limited
Category: otc | Type: HUMAN OTC DRUG LABEL
Date: 20121017

ACTIVE INGREDIENTS: alcohol 62 mL/100 mL
INACTIVE INGREDIENTS: Water; .ALPHA.-TOCOPHEROL ACETATE, D-; GLYCERIN; ALOE; PROPYLENE GLYCOL; CARBOMER 934; TROLAMINE

Drug Fact

Active Ingredient Purpose
Ethyl Alcohol 62% ********** Antiseptic

PURPOSE

Hand sanitizer to help decrease bacteria on the skin. when water, soap and towel are not available.
Recommended for repeat use

KEEP OUT OF REACH OF CHILDREN

In case of accidental ingestion, seek professional assistance or contact a Poison Control Center immediately.

INDICATIONS AND USAGE

put a thumb size amount in your palm and rub hands together briskly until dry.

WARNINGS

For external use only.
Flammable, keep away from fire or flame.
Do not apply around eyes; Do not use in ears and mouth.
When using this products, avoid contact with eyes. In case of contact, flush eyes with water.
Stop use and ask a doctor, if redness or irritation develop and persist for more than 72 hours.

Do not store in temperatures over 118°F

Children under 6 years of age should be supervised while using this products.

May discolor certain fabrics.

DOSAGE AND ADMINISTRATION

put a thumb size amount in your palm and rub hands together briskly until dry.

INACTIVE INGREDIENT

Water, Triethanolamine, Glycerin, Propylene glycol, Tocopheryl, Aloe Barbadensis gel, Carbomer, Fragrance